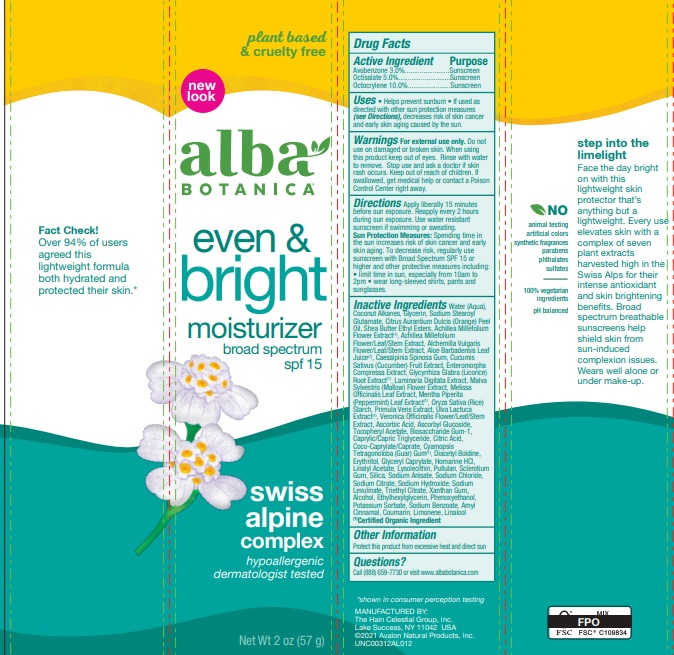 DRUG LABEL: Alba Botanica Even Advanced Moisturizer SPF15
NDC: 61995-3012 | Form: LOTION
Manufacturer: The Hain Celestial Group, Inc.
Category: otc | Type: HUMAN OTC DRUG LABEL
Date: 20231212

ACTIVE INGREDIENTS: OCTISALATE 5 g/100 g; OCTOCRYLENE 10 g/100 g; AVOBENZONE 3 g/100 g
INACTIVE INGREDIENTS: HYDROLYZED ULVA COMPRESSA PROTEIN (ACID; 300-5000 MW); PRUNELLA VULGARIS FLOWER; LINALOOL, (+)-; DIACETYL BOLDINE; LIMONENE, (+)-; CINNAMYLAMINE; COUMARIN; SODIUM LEVULINATE; TRIETHYL CITRATE; SODIUM BENZOATE; POTASSIUM SORBATE; SODIUM CHLORIDE; ASCORBYL GLUCOSIDE; CAESALPINIA SPINOSA RESIN; ERYTHRITOL; HOMARINE HYDROCHLORIDE; ETHYLHEXYLGLYCERIN; LAMINARIA DIGITATA; ULVA LACTUCA; SODIUM STEAROYL GLUTAMATE; ALCOHOL; PHENOXYETHANOL; ALOE VERA LEAF; GLYCERIN; WATER; .ALPHA.-TOCOPHEROL ACETATE; XANTHAN GUM; ASCORBIC ACID; ANHYDROUS CITRIC ACID; COCO-CAPRYLATE/CAPRATE; LINALYL ACETATE; LECITHIN, SUNFLOWER; PULLULAN; HYDRATED SILICA; CITRUS AURANTIUM FRUIT OIL; MALVA SYLVESTRIS FLOWER; MELISSA OFFICINALIS LEAF OIL; MENTHA PIPERITA LEAF; ORYZA SATIVA WHOLE; PRIMULA VERIS WHOLE; VERONICA OFFICINALIS WHOLE; CAPRYLIC/CAPRIC ACID; CYAMOPSIS TETRAGONOLOBA WHOLE; GLYCERYL CAPRATE; CLAVICEPS PURPUREA SCLEROTIUM; SODIUM ANISATE; SODIUM CITRATE; SODIUM HYDROXIDE; COCONUT ALKANES; BIOSACCHARIDE GUM-1; ACHILLEA MILLEFOLIUM FLOWER; ACHILLEA MILLEFOLIUM WHOLE; GLYCYRRHIZA GLABRA; SHEA BUTTER ETHYL ESTERS; CUCUMIS SATIVUS WHOLE

AL00312 Alba Botanica Even and Bright Moisturizer SPF 15
Formula 155-029A

ACTIVE INGREDIENT

Avobenzone 3.0%

Octisalate 5.0%

Octocrylene 10.0%

DOSAGE AND ADMINISTRATION

For sunscreen use apply liberally 15 minutes before sun exposure. Reapply at least every 2 hours. Use a water resistant sunscreen when swimming or sweating.

PURPOSE

Sunscreen

WARNINGS

For external use only. Do not use on damaged or broken skin. When using this product keep out of eyes. Rinse with water to remove. Stop use and ask a doctor if skin rash occurs.

Keep out of reach of children. If swallowed get medical help or contact Poison Center right away.

INACTIVE INGREDIENT

Water (Aqua), Coconut Alkanes, Glycerin, Sodium Stearoyl Glutamate, Citrus Aurantium Dulcis (Orange) Peel Oil, Shea Butter Ethyl Esters, Achillea Millefolium Flower Extract (1), Achillea Millefolium Flower/Leaf/Stem Extract, Alchemilla Vulgaris Flower/Leaf/Stem Extract, Aloe Barbadensis Leaf Juice (1), Caesalpinia Spinosa Gum, Cucumis Sativus (Cucumber) Fruit Extract, Enteromorpha Compressa Extract, Glycyrrhiza Glabra (Licorice) Root Extract (1), Laminaria Digitata Extract, Malva Sylvestris (Mallow) Flower Extract, Melissa Officinalis Leaf Extract, Mentha Piperita (Peppermint) Leaf Extract, Oryza Sativa (Rice) Starch, Primula Veris Extract, Ulva Lactuca Extract (1), Veronica Officinalis Flower/Leaf/Stem Extract, Ascorbic Acid, Ascorbyl Glucoside, Tocopheryl Acetate, Biosaccharide Gum-1, Caprylic/Capric Triglyceride, Citric Acid, Coco-Caprylate/Caprate, Cyamopsis Tetragonoloba (Guar) Gum (1), Diacetyl Boldine, Erythritol, Glyceryl Caprylate, Homarine HCl, Linalyl Acetate, Lysolecithin, Pullulan, Sclerotium Gum, Silica, Sodium Anisate, Sodium Chloride, Sodium Citrate, Sodium Hydroxide, Sodium Levulinate, Triethyl Citrate, Xanthan Gum, Alcohol, Ethylhexylglycerin, Phenoxyethanol, Potassium Sorbate, Sodium Benzoate, Amyl Cinnamal, Coumarin, Limonene, Linalool

(1) Certified Organicf Ingredient

INDICATIONS AND USAGE

Helps prevents sunburns. If used as directed with other sun protection measures, decreases risk of skin cancer and early skin aging caused by sun exposure. Skin Protection Measures: Spending time in the sun increases your risk of skin cancer and early skin aging. To decrease risk, regularly use sunscreen with Broad Spectrum SPF 15 or higher and other protective measures including: limit time in sun, especially from10am to 2pm, and wear long sleeved shirts, pants, hats and sunglases.